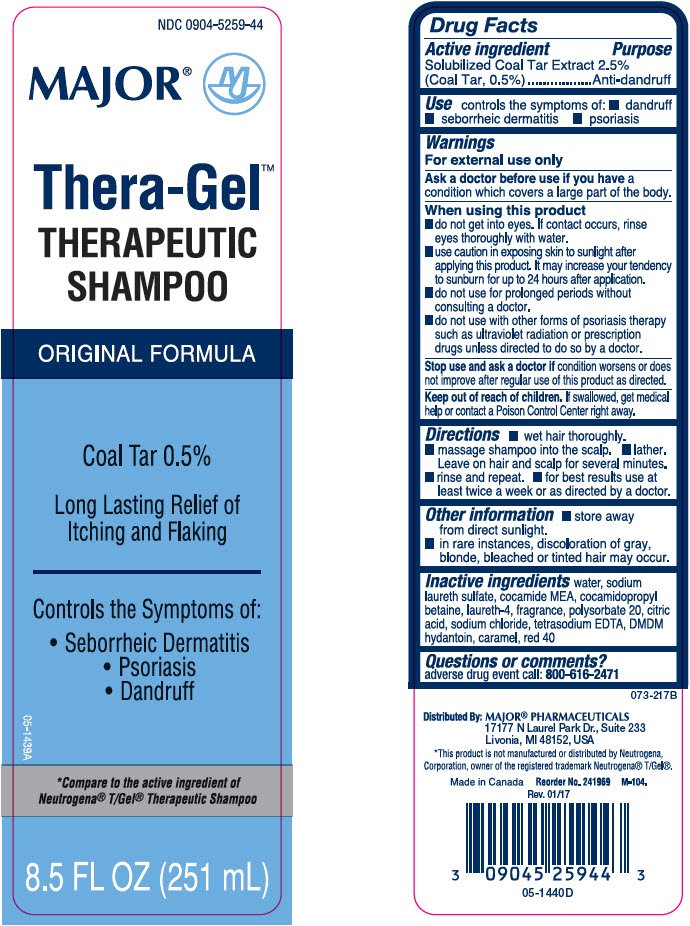 DRUG LABEL: CVS Health Vitamin A and D
NDC: 51316-399 | Form: OINTMENT
Manufacturer: CVS Health
Category: otc | Type: HUMAN OTC DRUG LABEL
Date: 20240528

ACTIVE INGREDIENTS: Lanolin 155 mg/1 g; Petrolatum 534 mg/1 g
INACTIVE INGREDIENTS: Cod Liver Oil; Soybean Lecithin; Microcrystalline Wax; Mineral Oil; Paraffin

Major® Thera-Gel™ Therapeutic
Anti-Dandruff

Drug Facts

Active ingredient

Solubilized Coal Tar Extract 2.50% (Coal Tar, 0.50%)

Purpose

Anti-dandruff, anti-seborrheic dermatitis, anti-psoriasis

Use

controls the symptom of:

- dandruff
- seborrheic dermatitis
- psoriasis

Warnings

For external use only.

Ask a doctor before use if you have a condition that covers a large area of the body.

When using this product

- avoid contact with the eyes. If contact occurs, rinse eyes thoroughly with water
- use caution in exposing skin to sunlight after applying this product. It may increase your tendency to sunburn for up to 24 hours after application.
- do not use for prolonged periods without consulting a doctor.
- do not use this product with other forms of psoriasis therapy such as ultraviolet radiation or prescription drugs unless directed to do so by a doctor.

Stop use and ask a doctor if condition worsens or does not improve after regular use of this product as directed.

Keep out of reach of children. If swallowed, get medical help or contact a Poison Control Center (1-800-222-1222) right away.

Directions

- for best results use at least twice a week or as directed by a doctor
- wet hair thoroughly
- massage shampoo into the scalp
- lather, leave on hair and scalp for several minutes.
- rinse and repeat

Other information

- store away from direct sunlight

- in rare instances, discoloration of gray, blonde, bleached or tinted hair may occur

Inactive ingredients

water, sodium laureth sulfate, cocamide MEA, cocamidopropyl betaine, laureth-4, fragrance, polysorbate 20, citric acid, sodium chloride, disodium EDTA, phenoxyethanol, methylchloroisothiazolinone, methylisothiazolinone, red 40, blue 1, yellow 5, yellow 6.

Questions or comments?

1-866-567-8600

Distributed By: MAJOR® PHARMACEUTICALS
17177 N Laurel Park Dr., Suite 233
Livonia, MI 48152, USA

PRINCIPAL DISPLAY PANEL - 251 mL Bottle Label

NDC 0904-5259-44

MAJOR®

Thera-Gel™
THERAPEUTIC
SHAMPOO

ORIGINAL FORMULA

Coal Tar 0.5%

Long Lasting Relief of
Itching and Flaking

Controls the Symptoms of:

- Seborrheic Dermatitis
- Psoriasis
- Dandruff

05-1439A

*Compare to the active ingredient of
Neutrogena® T/Gel® Therapeutic Shampoo

8.5 FL OZ (251 mL)